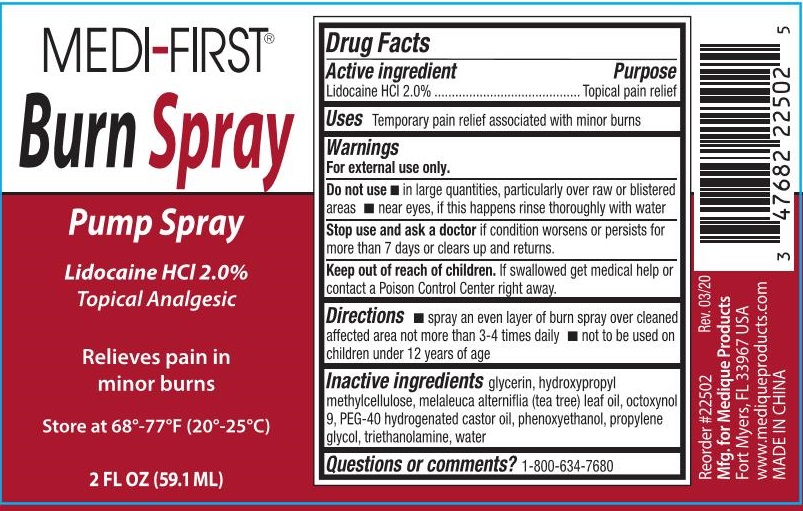 DRUG LABEL: Medi-First Burn
NDC: 47682-255 | Form: SPRAY
Manufacturer: Unifirst First Aid Corporation
Category: otc | Type: HUMAN OTC DRUG LABEL
Date: 20250908

ACTIVE INGREDIENTS: LIDOCAINE HYDROCHLORIDE 20 g/1 L
INACTIVE INGREDIENTS: TROLAMINE; PEG-40 CASTOR OIL; OCTOXYNOL 9; PHENOXYETHANOL; WATER; PROPYLENE GLYCOL; HYPROMELLOSES; GLYCERIN; TEA TREE OIL

Medi-First Burn Spray

Active ingredient

Lidocaine HCl 2.0%

Purpose

Topical pain relief

Uses

Temporary pain relief associated with minor burns

Warnings

For external use only.

Do not use

- in large quantities, particularly over raw or blistered areas
- near eyes, if this happens rinse thoroughly with water

Stop use and ask doctor if

condition worsens or persists for more than 7 days or clears up and returns.

Keep out of reach of children. If swallowed get medical help or contact a Poison Control Center right away.

Directions

- spray an even layer of burn spray over cleaned affected area not more than 3-4 times daily
- not to be used on children under 12 years of age

Inactive ingredients

glycerin, hydroxypropyl methylcellulose, melaleuca alterniflia (tea tree) leaf oil, octoxynol 9, PEG-40 hydronated castor oil, phenoxyethanol, propylene glycol, triethanolamine, water

Questions or comments? 1-800-634-7680

Medi-First Burn Spray Label

Medi-First°

Burn Spray

Pump Spray

Lidocaine HCl 2.0%

Topical Analgesic

Relieves pain in minor burns

Store at 68°-77°F (20°-25°C)

2 FL OZ (59.1 ML)